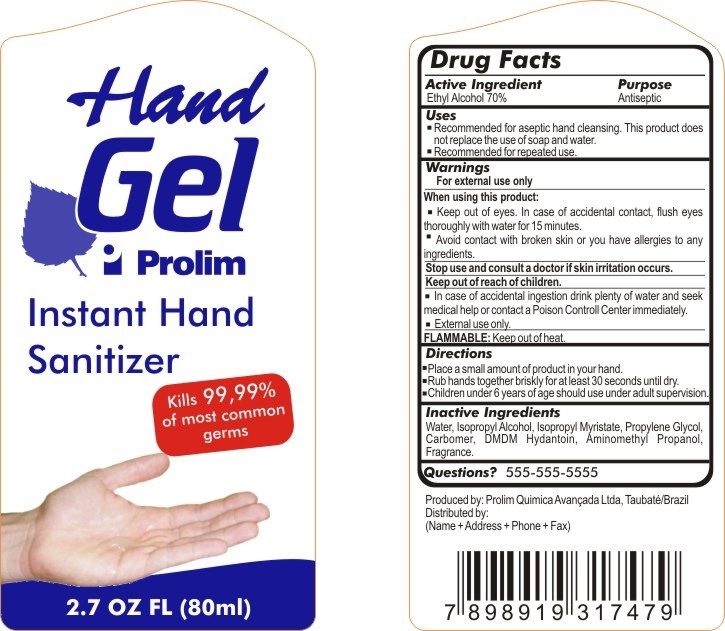 DRUG LABEL: Hand Gel Prolim Instant Hand Sanitizer
NDC: 50414-100 | Form: GEL
Manufacturer: Prolim Quimica Avancada Ltda.
Category: otc | Type: HUMAN OTC DRUG LABEL
Date: 20100215

ACTIVE INGREDIENTS: Alcohol 0.7 mg/1 mL

Drug Facts

Active Ingredient

Ethyl Alcohol 70%

Purpose

Antiseptic

Uses

- Recommended for aseptic hand cleansing. This product does not replace the use of soap and water.
- Recommended for repeated use.

Warnings

For external use only

When using this product

- Keep out of eyes. In case of accidental contact, flush eyes thoroughly with water for 15 minutes.
- Avoid contact with broken skin or you have allergies to any ingredients.

Stop use and consult a doctor if skin irritation occurs.

Keep out of reach of children

- In case of accidental ingestion drink plenty of water and seek medical help or contact a Poison Controll Center immediately.
- External use only.

FLAMMABLE: Keep out of heat.

Directions

- Place a small amount of product in your hand.
- Rub hands together briskly for at least 30 seconds until dry.
- Children under 6 years of age should use under adult supervision.

Inactive Ingredients

Water, Isopropyl Alcohol, Isopropyl Myristate, Propylene Glycol, Carbomer, DDM Hydantoin, Aminomethyl Propanol, Fragrance.

Questions?

555-555-5555

Principal Display Panel

HAND GEL PROLIM
INSTANT HAND SANITIZER
Kills 99,99% of most commom germs
2.7 OZ FL (80ml)